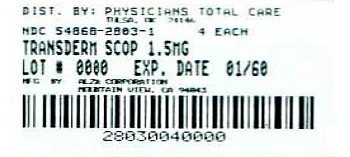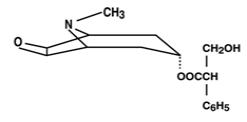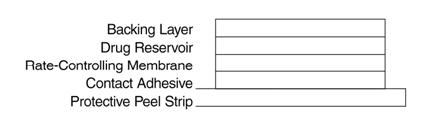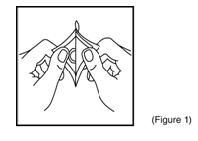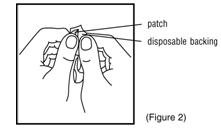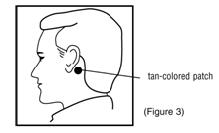 DRUG LABEL: Transderm Scop
NDC: 54868-2803 | Form: PATCH, EXTENDED RELEASE
Manufacturer: Physicians Total Care, Inc.
Category: prescription | Type: HUMAN PRESCRIPTION DRUG LABEL
Date: 20130326

ACTIVE INGREDIENTS: SCOPOLAMINE 1 mg/3 d
INACTIVE INGREDIENTS: POLYISOBUTYLENE (1100000 MW); POLYISOBUTYLENE (35000 MW); LIGHT MINERAL OIL; CHLOROFORM

Transderm Scōp

Transderm Scōp

scopolamine 1.5 mg

Transdermal Therapeutic System

Programmed to deliver in-vivo approximately 1.0 mg of scopolamine over 3 days

DESCRIPTION

The Transderm Scōp (transdermal scopolamine) system is a circular flat patch designed for continuous release of scopolamine following application to an area of intact skin on the head, behind the ear. Each system contains 1.5 mg of scopolamine base. Scopolamine is
a-(hydroxymethyl) benzeneacetic acid 9-methyl-3-oxa-9-azatricyclo [3.3.1.0^2,4] non-7-yl ester. The empirical formula is C17H21NO4 and its structural formula is

Scopolamine is a viscous liquid that has a molecular weight of 303.35 and a pKa of 7.55-7.81. The Transderm Scōp system is a film 0.2 mm thick and 2.5 cm^2, with four layers. Proceeding from the visible surface towards the surface attached to the skin, these layers are: (1) a backing layer of tan-colored, aluminized, polyester film; (2) a drug reservoir of scopolamine, light mineral oil, and polyisobutylene; (3) a microporous polypropylene membrane that controls the rate of delivery of scopolamine from the system to the skin surface; and (4) an adhesive formulation of mineral oil, polyisobutylene, and scopolamine. A protective peel strip of siliconized polyester, which covers the adhesive layer, is removed before the system is used. The inactive components, light mineral oil (12.4 mg) and polyisobutylene (11.4 mg), are not released from the system.

Cross section of the system:

CLINICAL PHARMACOLOGY

Pharmacology

The sole active agent of Transderm Scōp is scopolamine, a belladonna alkaloid with well-known pharmacological properties. It is an anticholinergic agent which acts: i) as a competitive inhibitor at postganglionic muscarinic receptor sites of the parasympathetic nervous system, and ii) on smooth muscles that respond to acetylcholine but lack cholinergic innervation. It has been suggested that scopolamine acts in the central nervous system (CNS) by blocking cholinergic transmission from the vestibular nuclei to higher centers in the CNS and from the reticular formation to the vomiting center^1,2. Scopolamine can inhibit the secretion of saliva and sweat, decrease gastrointestinal secretions and motility, cause drowsiness, dilate the pupils, increase heart rate, and depress motor function^2.

Pharmacokinetics

Scopolamine’s activity is due to the parent drug. The pharmacokinetics of scopolamine delivered via the system are due to the characteristics of both the drug and dosage form. The system is programmed to deliver in-vivo approximately 1.0 mg of scopolamine at an approximately constant rate to the systemic circulation over 3 days. Upon application to the post-auricular skin, an initial priming dose of scopolamine is released from the adhesive layer to saturate skin binding sites. The subsequent delivery of scopolamine to the blood is determined by the rate controlling membrane and is designed to produce stable plasma levels in a therapeutic range. Following removal of the used system, there is some degree of continued systemic absorption of scopolamine bound in the skin layers.

Absorption: Scopolamine is well-absorbed percutaneously. Following application to the skin behind the ear, circulating plasma levels are detected within 4 hours with peak levels being obtained, on average, within 24 hours. The average plasma concentration produced is 87 pg/mL for free scopolamine and 354 pg/mL for total scopolamine (free + conjugates).

Distribution: The distribution of scopolamine is not well characterized. It crosses the placenta and the blood brain barrier and may be reversibly bound to plasma proteins.

Metabolism: Although not well characterized, scopolamine is extensively metabolized and conjugated with less than 5% of the total dose appearing unchanged in the urine.

Elimination: The exact elimination pattern of scopolamine has not been determined. Following patch removal, plasma levels decline in a log linear fashion with an observed half-life of 9.5 hours. Less than 10% of the total dose is excreted in the urine as parent and metabolites over 108 hours.

Clinical Results: In 195 adult subjects of different racial origins who participated in clinical efficacy studies at sea or in a controlled motion environment, there was a 75% reduction in the incidence of motion-induced nausea and vomiting^3.

In two pivotal clinical efficacy studies in 391 adult female patients undergoing cesarean section or gynecological surgery with anesthesia and opiate analgesia, 66% of those treated with Transderm Scōp (compared to only 46% of those receiving placebo) reported no retching/vomiting within the 24-hour period following administration of anesthesia/opiate analgesia. When the need for additional antiemetic medication was assessed during the same period, there was no need for medication in 76% of patients treated with Transderm Scōp as compared to 59% of placebo-treated patients ^(4, 5).

INDICATIONS AND USAGE

Transderm Scōp is indicated in adults for prevention of nausea and vomiting associated with motion sickness and recovery from anesthesia and surgery. The patch should be applied only to skin in the postauricular area.

CONTRAINDICATIONS

Transderm Scōp is contraindicated in persons who are hypersensitive to the drug scopolamine or to other belladonna alkaloids, or to any ingredient or component in the formulation or delivery system, or in patients with angle-closure (narrow angle) glaucoma.

WARNINGS

Glaucoma therapy in patients with chronic open-angle (wide-angle) glaucoma should be monitored and may need to be adjusted during Transderm Scōp use, as the mydriatic effect of scopolamine may cause an increase in intraocular pressure.

Transderm Scōp should not be used in children and should be used with caution in the elderly. See PRECAUTIONS.

Since drowsiness, disorientation, and confusion may occur with the use of scopolamine, patients should be warned of the possibility and cautioned against engaging in activities that require mental alertness, such as driving a motor vehicle or operating dangerous machinery.

Rarely, idiosyncratic reactions may occur with ordinary therapeutic doses of scopolamine. The most serious of these that have been reported are: acute toxic psychosis, including confusion, agitation, rambling speech, hallucinations, paranoid behaviors, and delusions.

PRECAUTIONS

General

Scopolamine should be used with caution in patients with pyloric obstruction or urinary bladder neck obstruction. Caution should be exercised when administering an antiemetic or antimuscarinic drug to patients suspected of having intestinal obstruction.

Transderm Scōp should be used with caution in the elderly or in individuals with impaired liver or kidney functions because of the increased likelihood of CNS effects.

Caution should be exercised in patients with a history of seizures or psychosis, since scopolamine can potentially aggravate both disorders.

Skin burns have been reported at the patch site in several patients wearing an aluminized transdermal systems during a Magnetic Resonance Imaging scan (MRI). Because Transderm Scōp® contains aluminum, it is recommended to remove the system before undergoing an MRI.

Information for Patients

Since scopolamine can cause temporary dilation of the pupils and blurred vision if it comes in contact with the eyes, patients should be strongly advised to wash their hands thoroughly with soap and water immediately after handling the patch. In addition, it is important that used patches be disposed of properly to avoid contact with children or pets.

Patients should be advised to remove the patch immediately and promptly contact a physician in the unlikely event that they experience symptoms of acute narrow-angle glaucoma (pain and reddening of the eyes, accompanied by dilated pupils). Patients should also be instructed to remove the patch if they develop any difficulties in urinating.

Patients who expect to participate in underwater sports should be cautioned regarding the potentially disorienting effects of scopolamine. A patient brochure is available.

Drug Interactions

The absorption of oral medications may be decreased during the concurrent use of scopolamine because of decreased gastric motility and delayed gastric emptying.

Scopolamine should be used with care in patients taking other drugs that are capable of causing CNS effects such as sedatives, tranquilizers, or alcohol. Special attention should be paid to potential interactions with drugs having anticholinergic properties; e.g., other belladonna alkaloids, antihistamines (including meclizine), tricyclic antidepressants, and muscle relaxants.

Laboratory Test Interactions

Scopolamine will interfere with the gastric secretion test.

Carcinogenesis, Mutagenesis, Impairment of Fertility

No long-term studies in animals have been completed to evaluate the carcinogenic potential of scopolamine. The mutagenic potential of scopolamine has not been evaluated. Fertility studies were performed in female rats and revealed no evidence of impaired fertility or harm to the fetus due to scopolamine hydrobromide administered by daily subcutaneous injection. Maternal body weights were reduced in the highest-dose group (plasma level approximately 500 times the level achieved in humans using a transdermal system).

Pregnancy Category C

Teratogenic studies were performed in pregnant rats and rabbits with scopolamine hydrobromide administered by daily intravenous injection. No adverse effects were recorded in rats. Scopolamine hydrobromide has been shown to have a marginal embryotoxic effect in rabbits when administered by daily intravenous injection at doses producing plasma levels approximately 100 times the level achieved in humans using a transdermal system. During a clinical study among women undergoing cesarean section treated with Transderm Scōp in conjunction with epidural anesthesia and opiate analgesia, no evidence of CNS depression was found in the newborns. There are no other adequate and well-controlled studies in pregnant women. Other than in the adjunctive use for delivery by cesarean section, Transderm Scōp should be used in pregnancy only if the potential benefit justifies the potential risk to the fetus.

Nursing Mothers

Because scopolamine is excreted in human milk, caution should be exercised when Transderm Scōp is administered to a nursing woman.

Labor and Delivery

Scopolamine administered parenterally at higher doses than the dose delivered by Transderm Scōp does not increase the duration of labor, nor does it affect uterine contractions. Scopolamine does cross the placenta.

Pediatric Use

The safety and effectiveness of Transderm Scōp in children has not been established. Children are particularly susceptible to the side effects of belladonna alkaloids. Transderm Scōp should not be used in children because it is not known whether this system will release an amount of scopolamine that could produce serious adverse effects in children.

ADVERSE DRUG EXPERIENCES

The adverse reactions for Transderm Scōp are provided separately for patients with motion sickness and with post-operative nausea and vomiting.

Motion Sickness: In motion sickness clinical studies of Transderm Scōp, the most frequent adverse reaction was dryness of the mouth. This occurred in about two thirds of patients on drug. A less frequent adverse drug reaction was drowsiness, which occurred in less than one sixth of patients on drug. Transient impairment of eye accommodation, including blurred vision and dilation of the pupils, was also observed.

Post-operative Nausea and Vomiting: In a total of five clinical studies in which Transderm Scōp was administered perioperatively to a total of 461 patients and safety was assessed, dry mouth was the most frequently reported adverse drug experience, which occurred in approximately 29% of patients on drug. Dizziness was reported by approximately 12% of patients on drug^6.

Postmarketing and Other Experience: In addition to the adverse experiences reported during clinical testing of Transderm Scōp, the following are spontaneously reported adverse events from postmarketing experience. Because the reports cite events reported spontaneously from worldwide postmarketing experience, frequency of events and the role of Transderm Scōp in their causation cannot be reliably determined: acute angle-closure (narrow-angle) glaucoma; confusion; difficulty urinating; dry, itchy, or conjunctival injection of eyes; restlessness; hallucinations; memory disturbances; rashes and erythema; and transient changes in heart rate.

Drug Withdrawal/Post-Removal Symptoms: Symptoms such as dizziness, nausea, vomiting, and headache occur following abrupt discontinuation of antimuscarinics. Similar symptoms, including disturbances of equilibrium, have been reported in some patients following discontinuation of use of the Transderm Scōp system. These symptoms usually do not appear until 24 hours or more after the patch has been removed. Some symptoms may be related to adaptation from a motion environment to a motion-free environment. More serious symptoms including muscle weakness, bradycardia and hypotension may occur following discontinuation of Transderm Scōp.

OVERDOSAGE

Because strategies for the management of drug overdose continually evolve, it is strongly recommended that a poison control center be contacted to obtain up-to-date information regarding the management of Transderm Scōp patch overdose. The prescriber should be mindful that antidotes used routinely in the past may no longer be considered optimal treatment. For example, physostigmine, used more or less routinely in the past, is seldom recommended for the routine management of anticholinergic syndromes.

Until up-to-date authoritative advice is obtained, routine supportive measures should be directed to maintaining adequate respiratory and cardiac function.

The signs and symptoms of anticholinergic toxicity include: lethargy, somnolence, coma, confusion, agitation, hallucinations, convulsion, visual disturbance, dry flushed skin, dry mouth, decreased bowel sounds, urinary retention, tachycardia, hypertension, and supraventricular arrhythmias.

Most cases of toxicity involving the use of the product will resolve with simple removal of the patch. Serious symptomatic cases of overdosage involving multiple patch applications and/or ingestion may be managed by initially ensuring the patient has an adequate airway, and supporting respiration and circulation. This should be rapidly followed by removal of all patches from the skin and the mouth. If there is evidence of patch ingestion, gastric lavage, endoscopic removal of swallowed patches, or administration of activated charcoal should be considered, as indicated by the clinical situation. In any case where there is serious overdosage or signs of evolving acute toxicity, continuous monitoring of vital signs and ECG, establishment of intravenous access, and administration of oxygen are all recommended.

The symptoms of overdose/toxicity due to scopolamine should be carefully distinguished from the occasionally observed syndrome of withdrawal (see Drug Withdrawal/Post Removal Symptoms). Although mental confusion and dizziness may be observed with both acute toxicity and withdrawal, other characteristic findings differ: tachyarrhythmias, dry skin, and decreased bowel sounds suggest anticholinergic toxicity, while bradycardia, headache, nausea and abdominal cramps, and sweating suggest post-removal withdrawal. Obtaining a careful history is crucial to making the correct diagnosis.

DOSAGE AND ADMINISTRATION

Initiation of Therapy: To prevent the nausea and vomiting associated with motion sickness, one Transderm Scōp patch (programmed to deliver approximately 1.0 mg of scopolamine over 3 days) should be applied to the hairless area behind one ear at least 4 hours before the antiemetic effect is required. To prevent post operative nausea and vomiting, the patch should be applied the evening before scheduled surgery. To minimize exposure of the newborn baby to the drug, apply the patch one hour prior to cesarean section. Only one patch should be worn at any time. Do not cut the patch.

Handling: After the patch is applied on dry skin behind the ear, the hands should be washed thoroughly with soap and water and dried. Upon removal, the patch should be discarded. To prevent any traces of scopolamine from coming into direct contact with the eyes, the hands and the application site should be washed thoroughly with soap and water and dried. (A patient brochure is available).

Continuation of Therapy: Should the patch become displaced, it should be discarded, and a fresh one placed on the hairless area behind the other ear. For motion sickness, if therapy is required for longer than 3 days, the first patch should be removed and a fresh one placed on the hairless area behind the other ear. For perioperative use, the patch should be kept in place for 24 hours following surgery at which time it should be removed and discarded.

HOW SUPPLIED

The Transderm Scōp system is a tan-colored circular patch, 2.5 cm^2, on a clear, oversized, hexagonal peel strip, which is removed prior to use.

Each Transderm Scōp system contains 1.5 mg of scopolamine and is programmed to deliver in-vivo approximately 1.0 mg of scopolamine over 3 days. Transderm Scōp is available in packages of four patches. Each patch is foil wrapped. Patient instructions are included.

1 Package (4 patches) NDC 54868-2803-1

The system should be stored at controlled room temperature between 20°C-25°C (68°F-77°F).

Rx ONLY

REFERENCES

1. McEvoy, G.K. (ed.); AHSF Drug Information; American Society of Hospital Pharmacists, Bethesda, MD, pp. 608-611 (1990).
2. Gilman, A.G. et al (ed.); The Pharmacological Basis of Therapeutics (8th Ed.); Pergamon Press, New York, NY, pp. 150-165 (1990).
3. Pharmacokinetic Clinical data on file.
4. Kotelko, D.M. et al; “Transdermal scopolamine decreases nausea and vomiting following cesarean section in patients receiving epidural morphine”, Anesthesiology 71(5): 675-678 (1989).
5. Bailey, P.L. et al; “Transdermal scopolamine reduces nausea and vomiting after outpatient laparoscopy”, Anesthesiology 72(6): 977-980 (1990).
6. Clinical safety data on file.

Mfd by: ALZA Corporation

Mountain View, CA 94043

Distributed by:

Novartis Consumer Health, Inc.

Parsippany, NJ 07054-0622

©2006

42013C Printed in U.S.A. (Rev. 2/06)

Distributed by:
Physicians Total Care, Inc.
Tulsa, OK 74146

Patient Package Insert

Please read this instruction sheet care-fully before opening the system package.

Information for the Patient

Transderm Scōp

Generic Name: scopolamine,

pronounced skoe-POL-a-meen

Transdermal Therapeutic System

The Transderm Scōp system helps to prevent the nausea and vomiting of motion sickness for up to 3 days. It is a round adhesive patch that you place behind your ear several hours before you travel. It also helps to prevent the nausea and vomiting associated with the use of anesthesia and certain analgesics used during or after many types of surgery. If the patch is to be used in conjunction with scheduled surgery, it is applied the evening before surgery. For cesarean section, the patch is applied one hour prior to surgery to minimize exposure of the unborn child to the drug. Wear only one patch at any time.

Be sure to wash your hands thoroughly with soap and water immediately after handling the patch, so that any drug that might get on your hands will not come into contact with your eyes.

Avoid drinking alcohol while using Transderm Scōp. Also, be careful about driving or operating any machinery while using the system because the drug might make you drowsy.

DO NOT USE TRANSDERM SCŌP IF YOU ARE ALLERGIC TO SCOPOLAMINE.

TRANSDERM SCŌP SHOULD NOT BE USED IN CHILDREN AND SHOULD BE USED WITH CAUTION IN THE ELDERLY.

How the Transderm Scōp System Works

A group of nerve fibers deep inside the ear helps people keep their balance. For some people, the motion of ships, airplanes, trains, automobiles, and buses increases the activity of these nerve fibers. This increased activity causes the dizziness, nausea, and vomiting of motion sickness. People may have one, some, or all of these symptoms.

Transderm Scōp contains the drug scopolamine, which helps reduce the activity of the nerve fibers in the inner ear. When a Transderm Scōp patch is placed on the skin behind one of the ears, scopolamine passes through the skin and into the bloodstream. One patch may be kept in place for 3 days if needed.

It has been suggested that Transderm Scōp, when used to reduce nausea and vomiting associated with surgical anesthesia or analgesia, acts on the same nerve fibers that are affected when the product is taken for motion sickness.

Precautions

Before using Transderm Scōp, be sure to tell your doctor if you:

- Are pregnant or nursing (or plan to become pregnant)
- Have (or have had) glaucoma (increased pressure in the eyeball) or a predisposition to glaucoma
- Have (or have had) any metabolic, heart, liver, kidney, or other serious medical conditions
- Have any obstruction of the stomach or intestine
- Have any trouble urinating due to prostate enlargement or any bladder obstruction
- Have any allergy or have had a reaction such as a skin rash or redness to any drug, especially scopolamine, or chemical or food substance

Any of these conditions could make Transderm Scōp unsuitable for you. Also tell your doctor if you are taking any other medicines.

In the unlikely event that you experience pain in the eye and reddened whites of the eye while wearing the patch, which may be accompanied by widening of the pupil and blurred vision, remove the patch immediately and consult your doctor. As indicated below under Side Effects, widening of the pupils and blurred vision without pain or reddened whites of the eye is usually temporary and not serious.

Transderm Scōp should not be used in children. The safety of its use in children has not been determined. Children and the elderly may be particularly sensitive to the effects of scopolamine.

Skin burns have been reported at the patch site in several patients wearing an aluminized transdermal systems during a Magnetic Resonance Imaging scan (MRI). Because Transderm Scop® contains aluminum, it is recommended to remove the system before undergoing an MRI.

Side Effects

The most common side effect experienced by people using Transderm Scōp is dryness of the mouth. This occurs in about two thirds of the people. A less frequent side effect is drowsiness, which occurs in less than one sixth of the people. Temporary blurring of vision and dilation (widening) of the pupils may occur, especially if the drug is on your hands and comes in contact with the eyes. On infrequent occasions, disorientation, memory disturbances, dizziness, restlessness, hallucinations, confusion, difficulty urinating, skin rashes or redness, temporary changes in heart rate such as palpitations, dry itchy, or reddened whites of the eyes, and eye pain have been reported. If these effects do occur, remove the patch and call your doctor. Since drowsiness, disorientation, and confusion may occur with the use of scopolamine, be careful driving or operating any dangerous machinery, especially when you first start using the drug system.

In addition, if you plan to participate in underwater sports while wearing the patch, you should discuss with your doctor the potentially disorienting effects of scopolamine.

Eye Effects: Temporary blurring of vision and dilation (widening) of the pupils may occur, especially if the drug is on your fingers or hands and comes into contact with the eyes. Dry, itchy, or reddened whites of the eye and eye pain have been reported infrequently. In the unlikely event that you experience pain in the eye and reddened whites of the eye, which may be accompanied by widening of the pupil and blurred vision, remove the patch and consult your doctor promptly. Widening of the pupils and blurred vision without pain, or reddened whites of the eye, is usually temporary and not serious.

Drug Withdrawal/Post-Removal Symptoms: Symptoms such as dizziness, nausea, vomiting, headache, and disturbances of equilibrium have been reported by some people following discontinuation of use of the Transderm Scōp patch. These symptoms have occurred most often in people who have used the patches for more than 3 days, and frequently do not appear until 24 hours or more after the patch has been removed. These symptoms may be associated with adaptation from a motion environment to a motion-free environment. It is recommended that you consult with your doctor if these symptoms persist.

How to Use Transderm Scōp

Transderm Scōp should be stored at controlled room temperature between 20°C and 25°C (68°F and 77°F) until you are ready to use it.

1. For the prevention of motion sickness, plan to apply one Transderm Scōp patch at least 4 hours before you need it. If the patch is to be used in conjunction with scheduled surgery, it is applied the evening before surgery. For cesarean section, the patch is applied one hour prior to surgery to minimize exposure of the unborn child to the drug. Wear only one patch at any time. Do not cut the patch.
2. Select a hairless area of skin behind one ear, taking care to avoid any cuts or irritations. Wipe the area with a clean, dry tissue.
3. Cut along dotted line to open the pouch and then remove the patch (Figure 1).

1. Remove the clear plastic six-sided backing from the round patch. Try not to touch the adhesive surface on the patch with your hands (Figure 2).

1. Firmly apply the adhesive surface (metallic side) to the dry area of skin behind the ear so that the tan-colored side is showing (Figure 3). Make good contact, especially around the edge. Once you have placed the patch behind your ear, do not move it for as long as you want to use it (e.g., up to 3 days for prevention of motion sickness).

1. Important: After the patch is in place, be sure to wash your hands thoroughly with soap and water to remove any scopolamine. If this drug were to come into contact with your eyes, it could cause temporary blurring of vision and dilation (widening) of the pupils (the dark circles in the center of your eyes). Unless accompanied by eye pain and reddened whites of the eyes (see Precautions), this is not serious and your pupils should return to normal.
2. If the patch is being used to prevent the nausea and vomiting of motion sickness, remove the patch after 3 days and throw it away. (You may remove it sooner if you are no longer concerned about motion sickness). If the patch is being used to prevent nausea and vomiting associated with anesthesia or analgesia, the patch should be kept in place for 24 hours following surgery at which time it should be removed and discarded. After removing the patch, be sure to wash your hands and the area behind your ear thoroughly with soap and water. Since the patch will still contain some active ingredient after use, and to avoid accidental contact or ingestion by children or pets, fold the used patch in half with the sticky side together and dispose in the trash out of the reach of children and pets.
3. If you wish to control the nausea and vomiting of motion sickness for longer than 3 days, remove the first patch after 3 days and place a new one behind the other ear, repeating instructions 2 through 7.
4. Keep the patch dry, if possible, to prevent it from falling off. Limited contact with water, however, as in bathing or swimming, will not affect the system. In the unlikely event that the patch falls off, throw it away and put a new one behind the other ear.
5. Please inform your doctor if you are taking other medications, including over-the-counter medications.

This leaflet presents a summary of information about Transderm Scōp. If you would like more information or if you have any questions, ask your doctor or pharmacist. A more technical leaflet is available, written for your doctor. If you would like to read the leaflet, ask your pharmacist to show you a copy. You may need the help of your doctor or pharmacist to understand some of the information.

Mfd. by: ALZA Corporation

Mountain View, CA 94043

Distributed by:

Novartis Consumer Health, Inc.

Parsippany, NJ 07054-0622

©2006

42014C Printed in U.S.A. (Rev. 2/06)